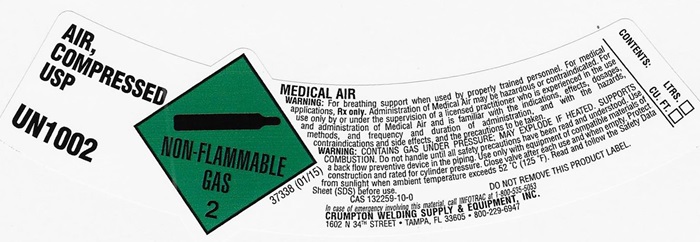 DRUG LABEL: AIR COMPRESSED
                
NDC: 52568-007 | Form: GAS
Manufacturer: Crumpton Welding Supply & Equipment, Inc.
Category: prescription | Type: HUMAN PRESCRIPTION DRUG LABEL
Date: 20241015

ACTIVE INGREDIENTS: OXYGEN 20 L/100 L
INACTIVE INGREDIENTS: NITROGEN 80 L/100 L

AIR COMPRESSED Product Label

AIR, COMPRESSED USP UN1002 NON-FLAMMABLE GAS 2 37338 (01/15)

MEDICAL AIR

WARNING: For breathing support when used by properly trained personnel. For medical applications. Rx only. Administration of Medical Air may be hazardous or contraindicated. For use only by or under the supervision of a licensed practitioner who is experienced in the use and administration of Medical Air and is familiar with the indications, effects, dosages, methods, and frequency and duration of administration, and with the hazards, contraindications and side effects and the precautions to be taken.

WARNING: CONTAINS GAS UNDER PRESSURE; MAY EXPLODE IF HEATED, SUPPORTS COMBUSION. Do not handle until all safety precautions have been read and understood. Use a backflow preventive device I the piping. Use only with equipment of compatible materials of construction and rated for cylinder pressure. Close valve after each use and when empty. Protect from sunlight when ambient temperature exceeds 52°C (125°F). Read and follow the Safety Data Sheet (SDS) before use.

CAS 132259-10-0 DO NOT REMOVE THIS PRODUCT LABEL.

In case of emergency involving this material call INFOTRAC at 1-800-535-5053

CRUMPTON WELDING SUPPLY & EQUIPMENT, INC.

162 N. 34th STREET • TAMPA, FL 33605 • 800-229-6947